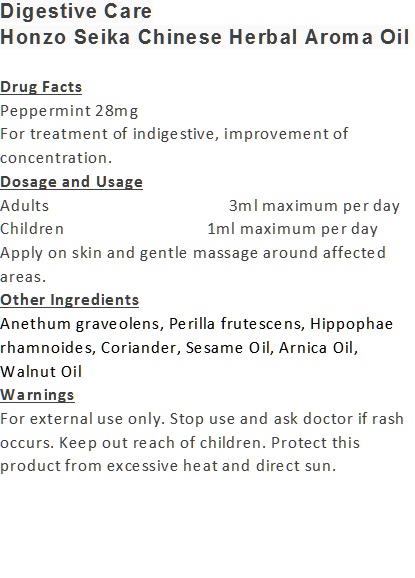 DRUG LABEL: Digestive Care
NDC: 71263-9906 | Form: OIL
Manufacturer: NIC CO., LTD.
Category: otc | Type: HUMAN OTC DRUG LABEL
Date: 20170101

ACTIVE INGREDIENTS: PEPPERMINT 28 mg/100 mL
INACTIVE INGREDIENTS: SESAME OIL; ANETHUM GRAVEOLENS WHOLE; WALNUT OIL; ARNICA MONTANA ROOT; PERILLA FRUTESCENS LEAF OIL; HIPPOPHAE RHAMNOIDES FRUIT OIL; CORIANDER OIL

Drug Facts

Peppermint 28mg

Use

For treatment of indigestive, improvement of concentration.

Dosage Suggestion

Adults 3ml maximum per day

Children 1ml maximum per day

Apply on skin and gentle massage around affected areas.

INACTIVE INGREDIENT

Other Ingredients

Anethum graveolens, Perilla frutescens, Hippophae rhamnoides, Coriander, Sesame Oil, Arnica Oil, Walnut Oil

Directions

Apply on skin and gentle massage around affected area.

Warnings

For external use only. Stop use and ask doctor if rash occurs. Keep out reach of children.

Other Information

Protect this product from excessive heat

and direct sun.

Warnings

For external use only. Stop use and ask doctor if rash occurs. Keep out reach of children.